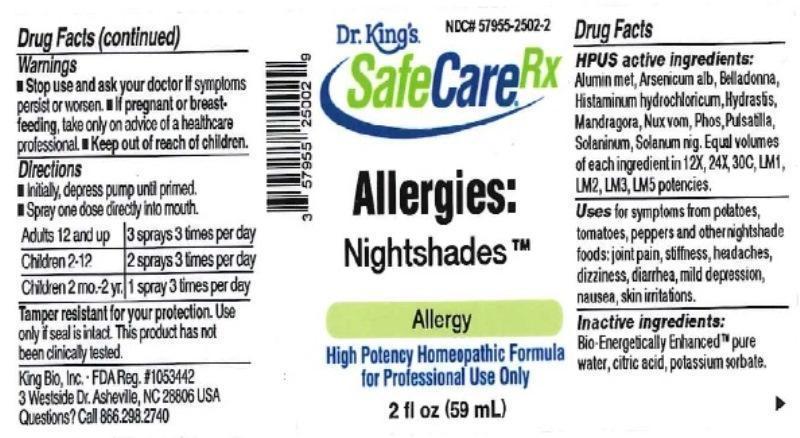 DRUG LABEL: Allergies Nightshades
NDC: 57955-2502 | Form: LIQUID
Manufacturer: King Bio Inc.
Category: homeopathic | Type: HUMAN OTC DRUG LABEL
Date: 20160401

ACTIVE INGREDIENTS: ALUMINUM 12 [hp_X]/12 mL; ARSENIC TRIOXIDE 12 [hp_X]/12 mL; ATROPA BELLADONNA 12 [hp_X]/12 mL; HISTAMINE DIHYDROCHLORIDE 12 [hp_X]/12 mL; GOLDENSEAL 12 [hp_X]/12 mL; MANDRAGORA OFFICINARUM ROOT 12 [hp_X]/12 mL; STRYCHNOS NUX-VOMICA SEED 12 [hp_X]/12 mL; PHOSPHORUS 12 [hp_X]/12 mL; PULSATILLA VULGARIS 12 [hp_X]/12 mL; SOLANINE 12 [hp_X]/12 mL; SOLANUM NIGRUM WHOLE 12 [hp_X]/12 mL
INACTIVE INGREDIENTS: WATER; ANHYDROUS CITRIC ACID; POTASSIUM SORBATE

Allergies: Nightshades™

ACTIVE INGREDIENT

Drug Facts__________________________________________________________________________________________________________

HPUS active ingredients: Aluminium metallicum, Arsenicum album, Belladonna, Histaminum hydrochloricum, Hydrastis canadensis, Mandragora officinarum, Nux vomica, Phosphorus, Pulsatilla, Solaninum, Solanum nigrum. Equal volumes of each ingredient in 12X, 24X, 30C, LM1, LM2, LM3, LM5 potencies.

INDICATIONS AND USAGE

Uses for symptoms from potatoes, tomatoes, peppers and other nightshade foods: joint pain, stiffness, headaches, dizziness, diarrhea, mild depression, nausea, skin irritations.

Inactive Ingredients:

Bio-Energetically Enhanced™ pure water, citric acid and potassium sorbate.

Warnings

- Stop use and ask your doctor if symptoms persist or worsen.
- If pregnant or breast-feeding, take only on advice of a healthcare professional.

- Keep out of reach of children.

Directions

- Initially, depress pump until primed.
- Spray one dose directly into mouth.
- Adults 12 and up: 3 sprays 3 times per day.
- Children 2-12: 2 sprays 3 times per day.
- Children 2 mo-2yr: 1 spray 3 times per day.

OTHER SAFETY INFORMATION

Tamper resistant for your protection. Use only if safety seal is intact. This product has not been clinically tested.

PURPOSE

Uses for symptoms from potatoes, tomatoes, peppers and other nightshade foods:

- joint pain
- stiffness
- headaches
- dizziness
- diarrhea
- mild depression
- nausea
- skin irritations